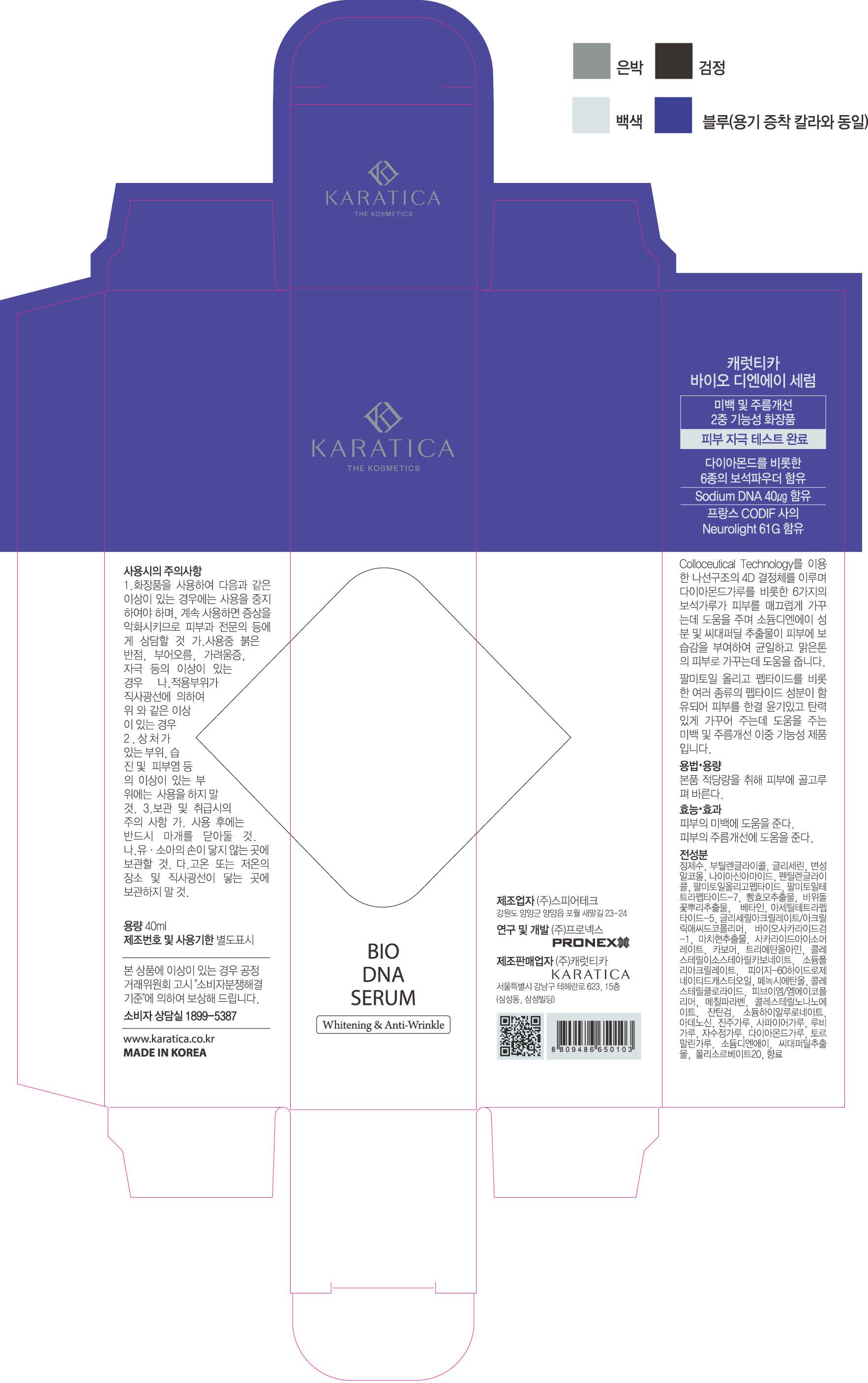 DRUG LABEL: Bio DNA Serum
NDC: 70514-0006 | Form: LIQUID
Manufacturer: Karatica Co., Ltd
Category: otc | Type: HUMAN OTC DRUG LABEL
Date: 20171207

ACTIVE INGREDIENTS: GLYCERIN 10.82 g/100 mL
INACTIVE INGREDIENTS: NIACINAMIDE; ADENOSINE

ACTIVE INGREDIENT

Glycerin

INACTIVE INGREDIENT

Niacinamide, Adenosine, DNA, All 6 Jewels, etc.

PURPOSE

Multi-Function - Wrinkle, Brightening, Moisturizing

keep out or reach of the children

INDICATIONS AND USAGE

Take appropriate amount and evenly apply it to the skin

WARNINGS

If you experience following symptoms after using the cosmetics, you should immediately stop using the cosmetics. If you continue to use them, the symptoms may worsen. Consult with your dermatologist.
A) When you experience red spots, swelling, itchiness and irritation while applying the product.
B) When the applied area experience symptoms while it is exposed to direct sunlight
2. Do not use the cosmetics on the areas where you have wounds, eczema or dermatitis
3. Precautions when storing and using the product
A) Keep the lid closed after using the product
B) Store it out of reach of children
C) Do not store it in places with high or low temperature or where it is exposed to the sunlight directly.

DOSAGE AND ADMINISTRATION

for external use only